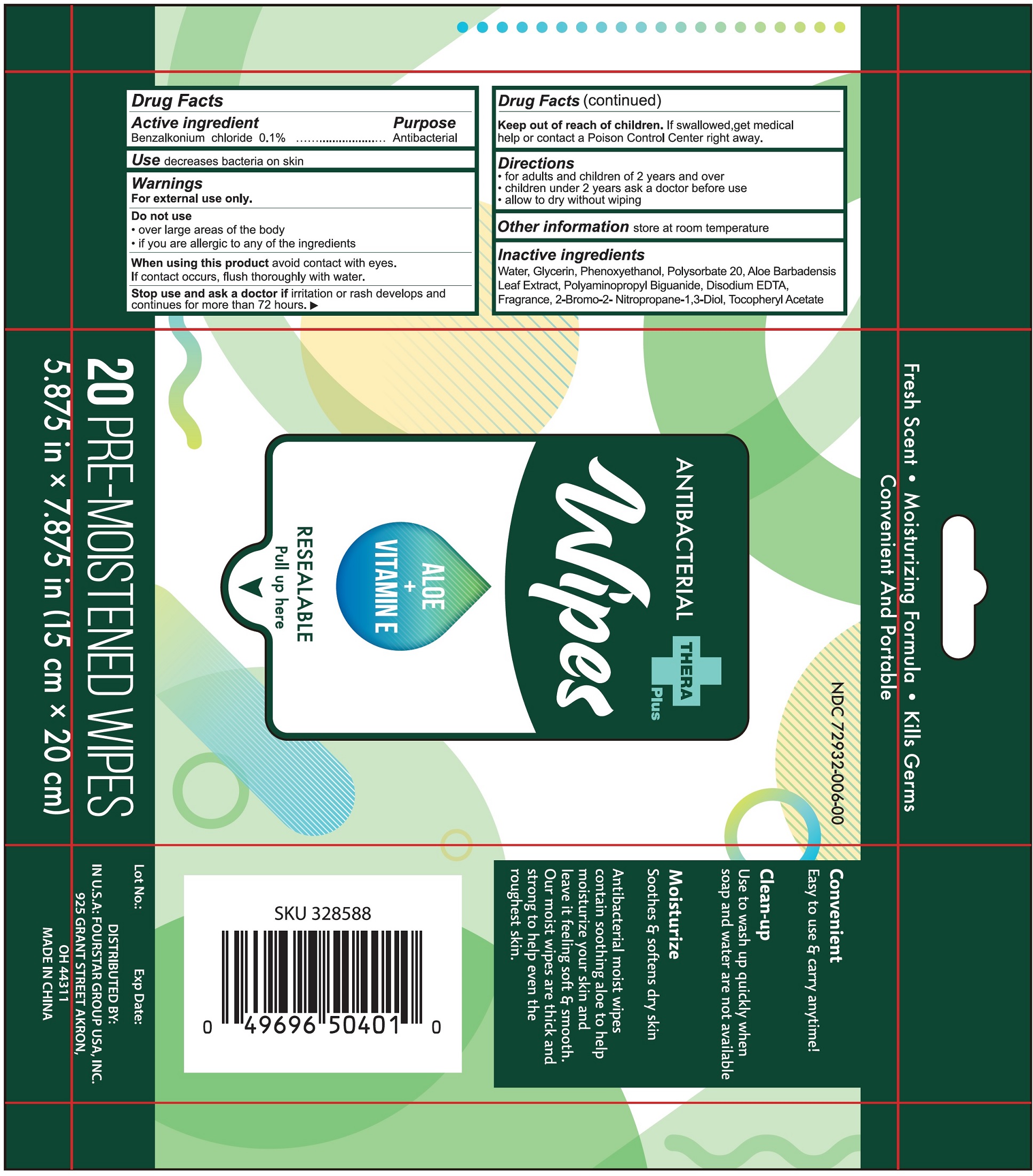 DRUG LABEL: Theraplus Antibacterial Wipes Fresh Scent with Aloe and Vitamin E
NDC: 80684-007 | Form: CLOTH
Manufacturer: Fourstar Group USA, Inc.
Category: otc | Type: HUMAN OTC DRUG LABEL
Date: 20231026

ACTIVE INGREDIENTS: BENZALKONIUM CHLORIDE 1 mg/1 mL
INACTIVE INGREDIENTS: WATER; GLYCERIN; PHENOXYETHANOL; POLYSORBATE 20; ALOE VERA LEAF; POLYAMINOPROPYL BIGUANIDE; EDETATE DISODIUM ANHYDROUS; BRONOPOL; .ALPHA.-TOCOPHEROL ACETATE

Theraplus Antibacterial Wipes Fresh Scent with Aloe and Vitamin E

Active ingredient

Benzalkonium chloride 0.1%

Purpose

Antibacterial

Use

decreases bacteria on skin

Warnings

For external use only.

Do not use

- over large areas of the body
- if you are allergic to any of the ingredients

When using this product

avoid contact with eyes. If contact occurs, flush thoroughly with water.

Stop use and ask a doctor if

irritation or rash develops and continues for more than 72 hours.

Keep out of reach of children.

If swallowed, get medical help or contact a Poison Control Center right away.

Directions

- for adults and children of 2 years and over
- children under 2 year ask a doctor before use
- allow to dry without wiping

Other information

store at room temperature

Inactive ingredients

Water, Glycerin, Phenoxyethanol, Polysorbate 20, Aloe Barbadensis Leaf Extract, Polyaminopropyl Biguanide, Disodium EDTA, Fragrance, 2-Bromo-2-Nitropropane-1,3-Diol, Tocopheryl Acetate